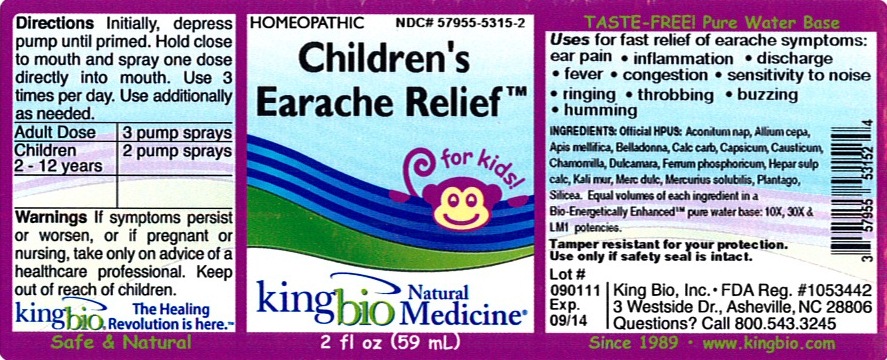 DRUG LABEL: Childrens Earache Relief
NDC: 57955-5315 | Form: LIQUID
Manufacturer: King Bio Inc.
Category: homeopathic | Type: HUMAN OTC DRUG LABEL
Date: 20120413

ACTIVE INGREDIENTS: ACONITUM NAPELLUS 10 [hp_X]/59 mL; ONION 10 [hp_X]/59 mL; APIS MELLIFERA 10 [hp_X]/59 mL; ATROPA BELLADONNA 10 [hp_X]/59 mL; OYSTER SHELL CALCIUM CARBONATE, CRUDE  10 [hp_X]/59 mL; CAPSICUM 10 [hp_X]/59 mL; CAUSTICUM 10 [hp_X]/59 mL; MATRICARIA RECUTITA 10 [hp_X]/59 mL; SOLANUM DULCAMARA TOP 10 [hp_X]/59 mL; FERROSOFERRIC PHOSPHATE 10 [hp_X]/59 mL; CALCIUM SULFIDE 10 [hp_X]/59 mL; POTASSIUM CHLORIDE 10 [hp_X]/59 mL; CALOMEL 10 [hp_X]/59 mL; MERCURIUS SOLUBILIS 10 [hp_X]/59 mL; PLANTAGO MAJOR 10 [hp_X]/59 mL; SILICON DIOXIDE 10 [hp_X]/59 mL
INACTIVE INGREDIENTS: WATER

Children's Earache Relief

Active Ingredients

Official HPUS: Aconitum napellus, Allium capa, Apis mellifica, Belladonna, Calcarea carbonica, Capsicum annuum, Causticum, Chamomilla, Dulcamara, Ferrum phosphoricum, Hepar sulphuris calcareum, Kali muriaticum, Mercurius dulcis, Mercurius solubilis, Plantago major, and Silicea.

Reference image childrens earache.jpg

Inactive Ingredient

Equal volumes of each ingredient in a Bio-Energetically Enhanced pure water base: 10X, 30X, and LM1 potencies.

Reference image childrens earache.jpg

Dosage and Administration

Directions: Initially, depress pump until primed. Hold close to mouth and spray one dose directly into mouth. Use 3 times per day. Use additionally as needed.

Adult Dose 3 pump sprays

Children 2-12 years 2 pump sprays

Reference image childrens earache.jpg

Purpose

Uses for fast relief of earache symptoms:

- ear pain
- inflammation
- discharge
- fever
- congestion
- sensitivity to noise
- ringing
- throbbing
- buzzing
- humming

Reference image childrens earache.jpg

Warnings

If symptoms persist or worsen, or if pregnant or nursing, take only on advice of a healthcare professional. Keep out of reach of children.

Other: Tamper resistant for your protection. Use only if safety seal is intact.

Reference image childrens earache.jpg

Keep out of reach of children.

Reference image childrens earache.jpg

Indications and Usage

Uses for fast relief of earache symptoms: ear pain, inflammation, discharge, fever, congestion, sensitivity to noise, ringing, throbbing, buzzing, and humming.

Reference image childrens earache.jpg

PACKAGE LABEL

King Bio Inc.

3 Westside Drive

Asheville, NC 28806

Questions? Call 800.543.3245

www.kingbio.com